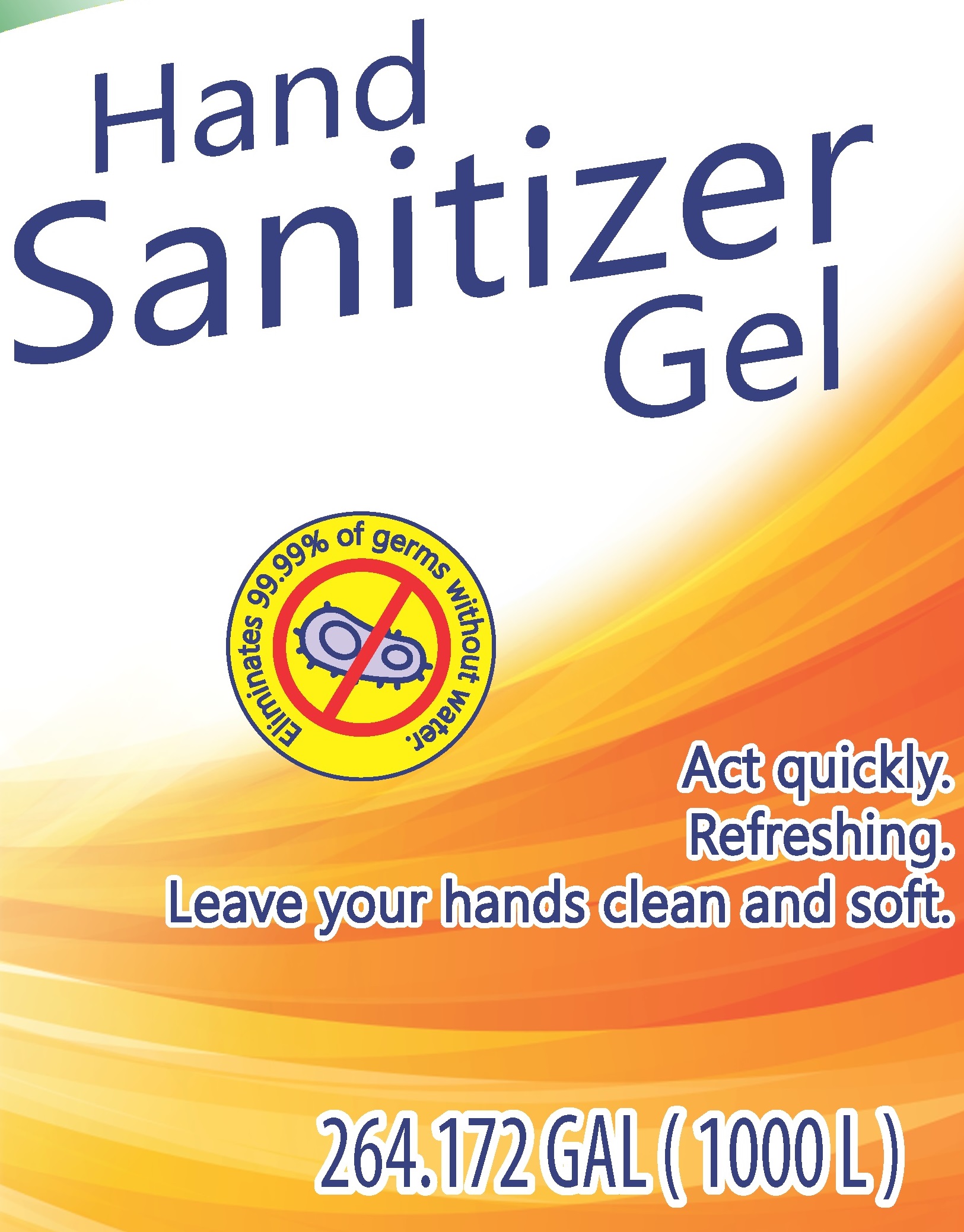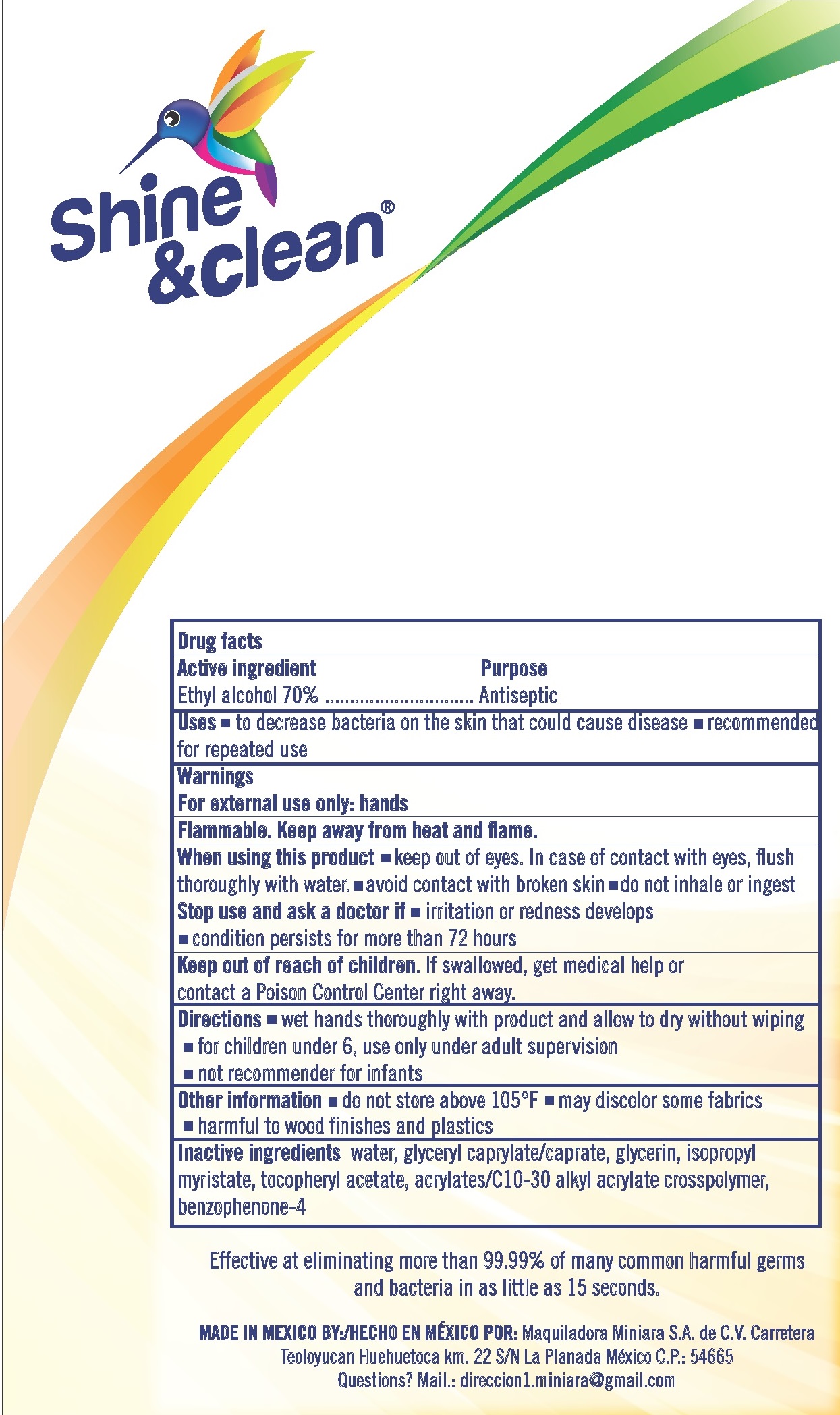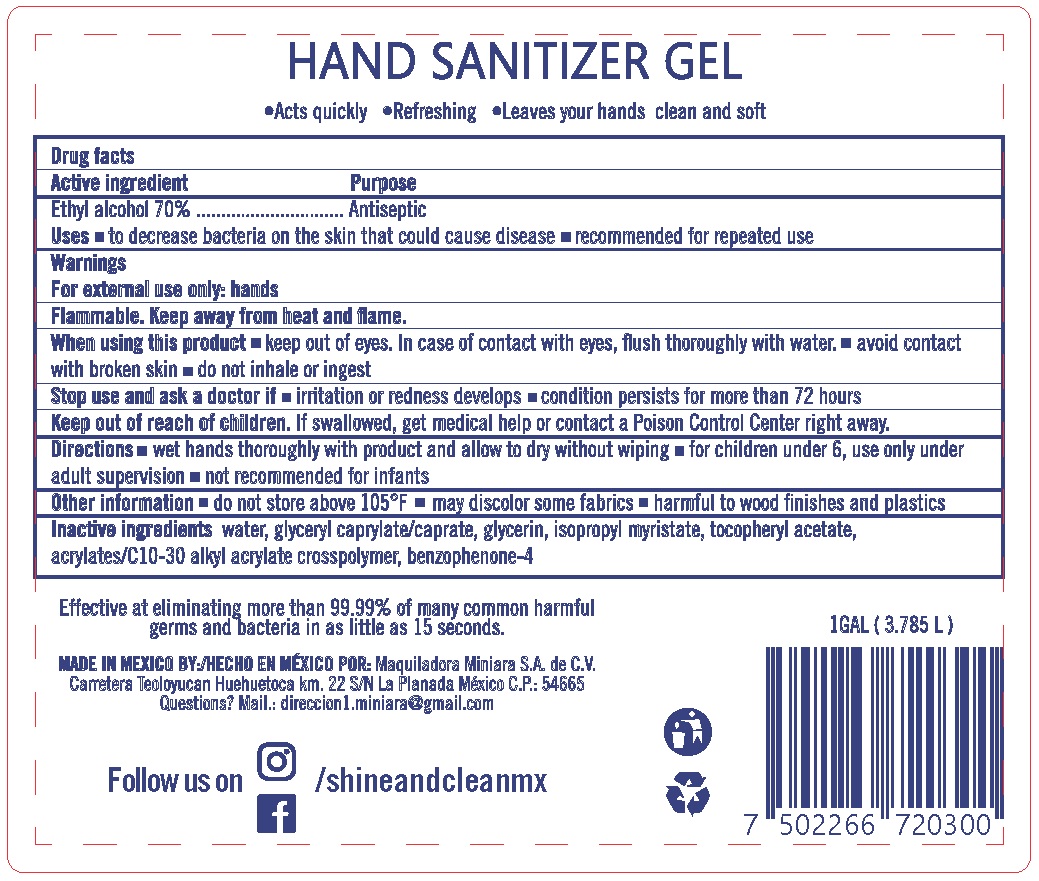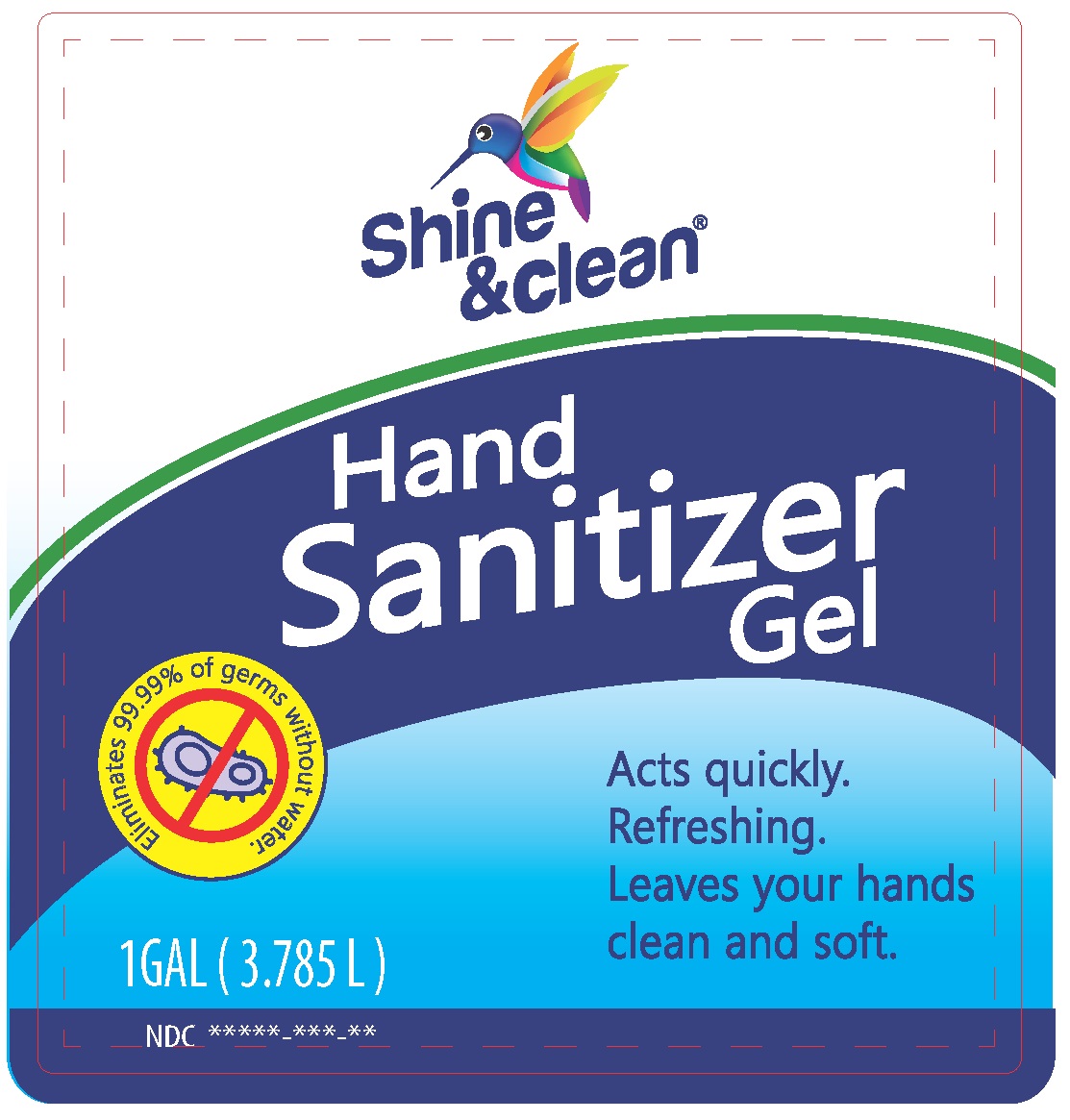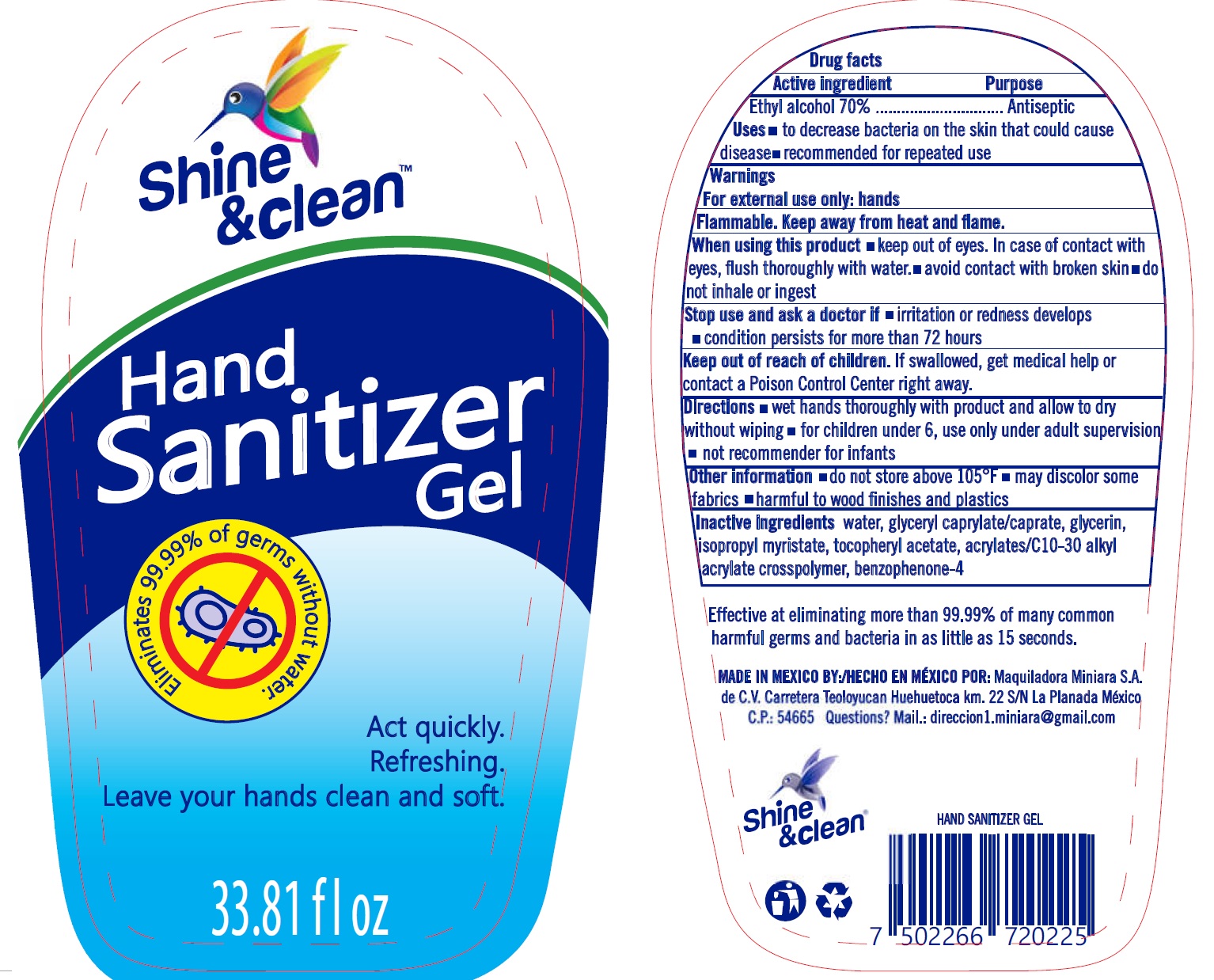 DRUG LABEL: Shine and Clean Hand Sanitizer
NDC: 76753-001 | Form: GEL
Manufacturer: Maquiladora Miniara S.A de C.V.
Category: otc | Type: HUMAN OTC DRUG LABEL
Date: 20200616

ACTIVE INGREDIENTS: ALCOHOL 0.7 mL/1 mL
INACTIVE INGREDIENTS: WATER; GLYCERYL MONOCAPRYLOCAPRATE; GLYCERIN; ISOPROPYL MYRISTATE; .ALPHA.-TOCOPHEROL ACETATE; CARBOMER INTERPOLYMER TYPE A (ALLYL SUCROSE CROSSLINKED); SULISOBENZONE

Shine and Clean Hand Sanitizer Gel

Active ingredient

Ethyl alcohol 70%

Purpose

Antiseptic

Uses

- to decrease bacteria on the skin that could cause disease
- recommended for repeated use

Warnings

For external use only: hands

Flammable. Keep away from heat and flame.

When using this product

- keep out of eyes. In case of contact with eyes, flush thoroughly with water.
- avoid contact with broken skin
- do not inhale or ingest

Stop use and ask a doctor if

- irritation or redness develops
- condition persists for more than 72 hours

Keep out of reach of children.

If swallowed, get medical help or contact a Poison Control Center right away.

Directions

- wet hands thoroughly with product and allow to dry without wiping
- for children under 6, use only under adult supervision
- not recommender for infants

Other information

- do not store above 105°F
- may discolor some fabrics
- harmful to wood finishes and plastics

Inactive ingredients

water, glyceryl caprylate/caprate, glycerin, isopropyl myristate, tocopheryl acetate, acrylates/C10-30 alkyl acrylate crosspolymer, benzophenone-4